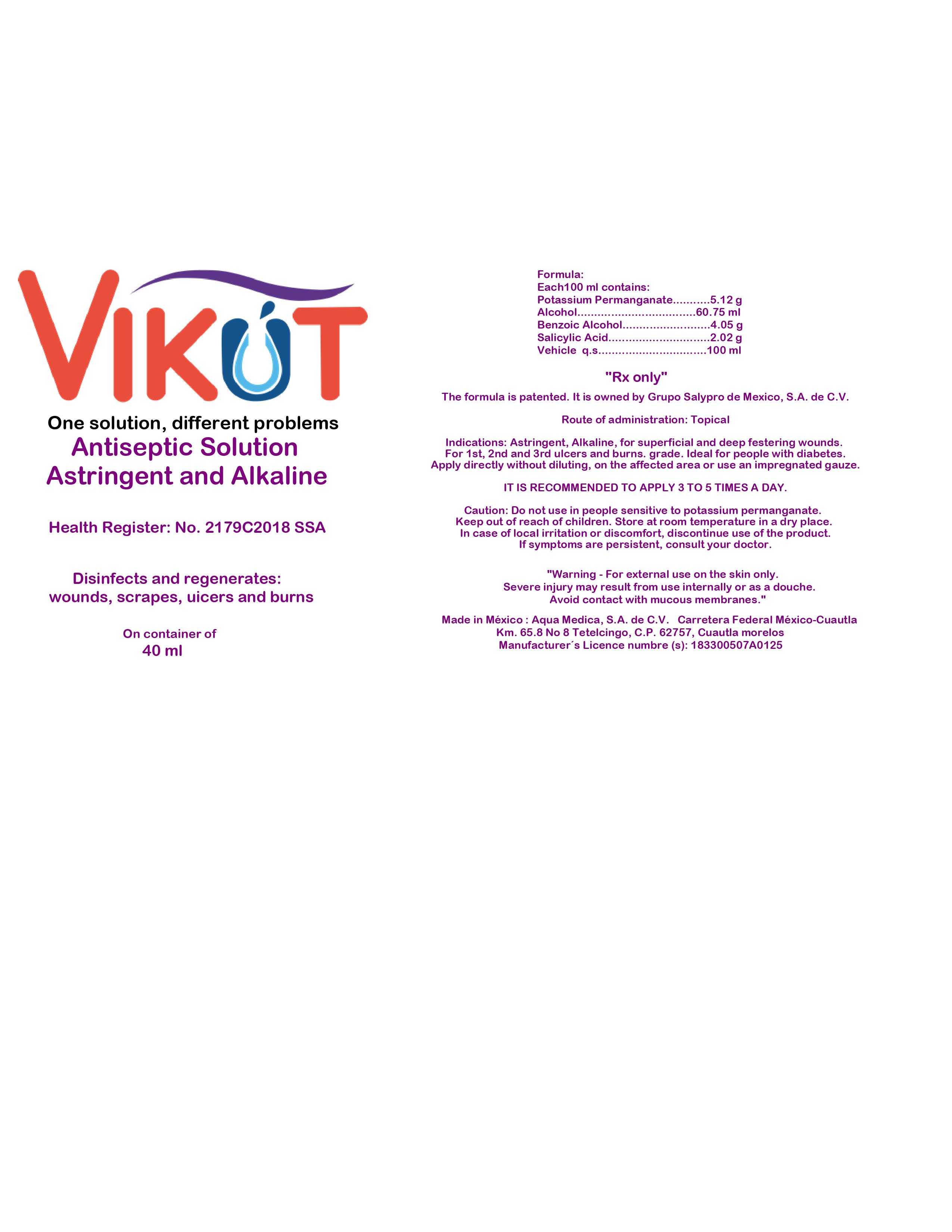 DRUG LABEL: Antiseptic Solution
NDC: 81760-310 | Form: SOLUTION
Manufacturer: Grupo Salypro de Mexico, S.A. de C.V.
Category: prescription | Type: HUMAN PRESCRIPTION DRUG LABEL
Date: 20220110

ACTIVE INGREDIENTS: POTASSIUM PERMANGANATE 5.12 g/100 g
INACTIVE INGREDIENTS: WATER 28.06 g/100 g; METHYL ALCOHOL 60.75 g/100 g; ACETYLSALICYLSALICYLIC ACID 2.02 g/100 g; .ALPHA.-(.ALPHA.-AMINOPROPYL)BENZYL ALCOHOL 4.05 g/100 g

These highlights do not include all the information needed to use VIKUT safely and effectively. See full prescribing information for www.vikutsolution.com

WARNING

For external use on the skin only.
Severe injury may result from use internally or as a douche. Avoid contact with mucous membranes."

INDICATIONS AND USAGE

Astringent, Alkaline, for superficial and deep festering wounds. for 1st, 2nd and 3rd ulcers and burns. grade. Ideal for people with diabetes.Úpply directly without diluting, on the affected area or use an impregnated gauze.

DOSAGE AND ADMINISTRATION

It Is Recommended to apply 3 to 5 times a day.

DOSAGE FORMS AND STRENGTHS

Antiseptic Solution 40ml

CONTRAINDICATIONS

Allergy or hypersensitivity to the active ingredient.

WARNINGS AND PRECAUTIONS

There may be moderate burning or pain after the first applications of the solution, which usually disappear with the continuation of the treatment.

DRUG INTERACTIONS

Free drug interactions. No patient presented adverse events related to treatment with Vikút®.

USE IN SPECIFIC POPULATIONS

VIKÚT solution is indicated for pre and post-operative antisepsis and the delimitation of the surgical field. Antisepsis of minor and deep wounds, burns (1, 2, and 3rd degree), lacerations, pyoderma, acne and bacterial and fungal infections of the skin, scalp. In wounds where it is desired to accelerate the healing process such as traumatic surgical wounds, episiotomies, varicose ulcers, decubitus ulcers, where in addition to accelerating the healing process it is desired to eliminate or prevent the presence of pathogenic germs that could delay the process healing.

LABEL

81760-310-01 40 mL Solution